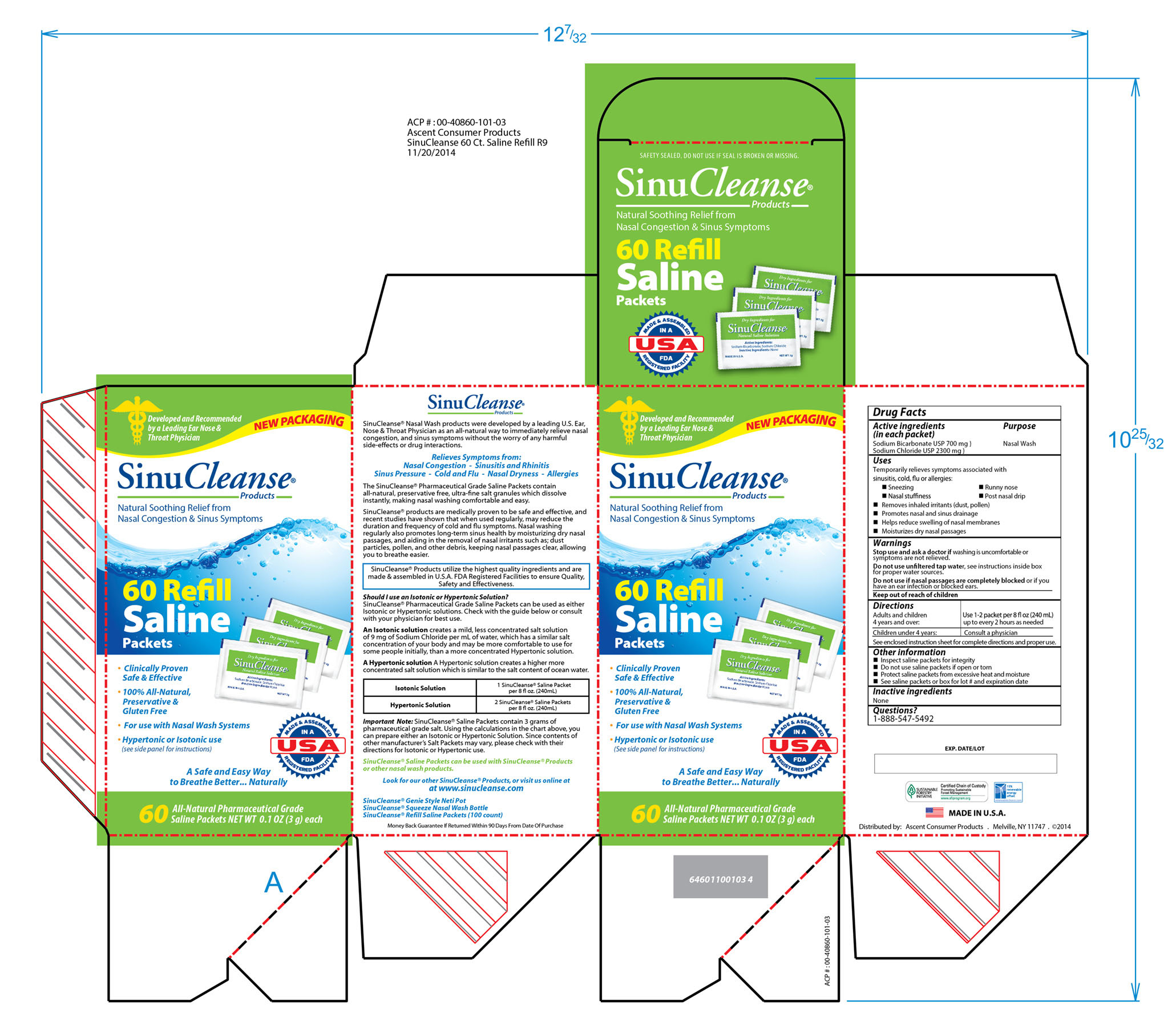 DRUG LABEL: SinuCleanse
NDC: 42829-408 | Form: POWDER, FOR SOLUTION
Manufacturer: ASCENT CONSUMER PRODUCTS, INC.
Category: otc | Type: HUMAN OTC DRUG LABEL
Date: 20251210

ACTIVE INGREDIENTS: SODIUM BICARBONATE 22.2 mg/100 mg; SODIUM CHLORIDE 77.8 mg/100 mg
INACTIVE INGREDIENTS: WATER

SinuCleanse

Active Ingredients

(in each packet)

Sodium Bicarbonate USP 700 mg

Sodium Chloride USP 2300 mg

Purpose

Nasal Wash

Uses

Temporarily relieves symptoms associated with

sinusitis, cold, flu or allergies:

-Sneezing

-Runny nose

-Nasal stuffiness

-Post nasal drip

-Removes inhaled irritants (dust, pollen)

-Promotes nasal and sinus drainage

-Helps reduce swelling of nasal membranes

-Moisturizes dry nasal passages

Warnings

Stop use and ask a doctor if washing is uncomfortable or symptoms

are not relieved.

Do not use unfiltered tap water, see instructions inside box

for proper water sources.

Do not use if nasal passages are completely blocked or if you have

an ear infection or blocked ears.

When using this product:

-Use by only one person

-Wash with soap and water after each use

-Top rack of dishwasher safe

-Do not heat in microwave

Keep out of reach of children

Directions

Adults and children 4 years and over: use 1/2 - 1 packet per 4 fl oz (120 mL)up to every two hours as needed

Children under 4 years: Consult a physician

See enclosed instruction sheet for complete directions and proper use

Other Information

-Inspect saline packets for integrity

-Do not use saline packets if open or torn

-Protect saline packets from excessive heat and moisture

-See saline packets or box for lot # and expiration date

Inactive Ingredients

None

Questions?

1-888-547-5492